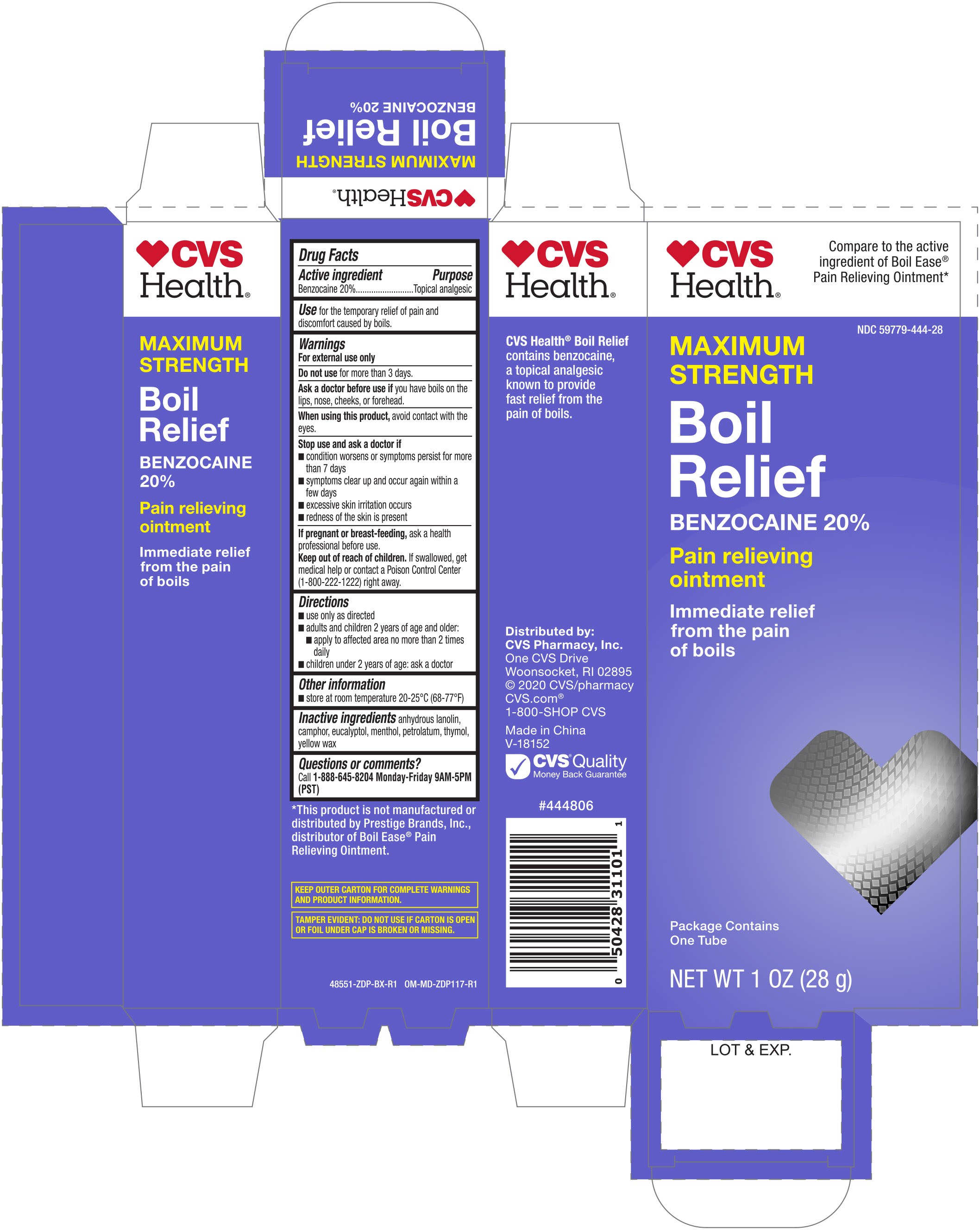 DRUG LABEL: CVS Maximum Strength Boil Relief
NDC: 59779-444 | Form: OINTMENT
Manufacturer: CVS Pharmacy, Inc.
Category: otc | Type: HUMAN OTC DRUG LABEL
Date: 20251030

ACTIVE INGREDIENTS: BENZOCAINE 20 g/100 g
INACTIVE INGREDIENTS: YELLOW WAX; CAMPHOR (SYNTHETIC); EUCALYPTUS OIL; LANOLIN; MENTHOL; THYMOL; PETROLATUM

CVS Boil Relief Ointment 1 oz 48551 ZDP

Active ingredient Purpose

Benzocaine 20%..................................... Pain Reliever

PURPOSE

Uses for the temporary relief of pain and discomfort caused by boils

Warnings

For external use only

Do not use for more than 3 days

Ask a doctor before use if you have boils on the lips, nose, cheeks, or forehead

When using this product avoid contact with the eyes

Stop use and ask a doctor if

- fever occurs
- redness around the boil develops
- condition worsens or does not improve
- symptoms presist for more than 3 days
- symptoms clear up and occur again within a few days

KEEP OUT OF REACH OF CHILDREN

Keep out of the reach of children. If swallowed, get medical help or contact a Poison Control Center right away.

Directions

Adults and children 2 years of age and older- apply to affected area no more than 2 times daily

Children under 2 years of age- consult a doctor

Other information

Keep carton for full drug facts

Inactive ingredients

anhydrous lanolin, camphor, eucalyptol, menthol, petrolatum, thymol, yellow wax

DOSAGE AND ADMINISTRATION

DISTRIBUTED BY:

CVS PHARMACY, INC.

ONE CVS DRIVE

WOONSOCKET, RI 02895